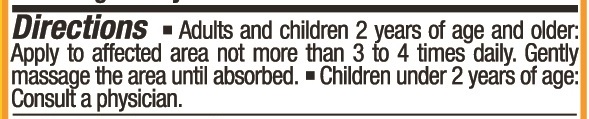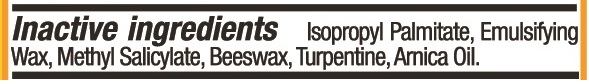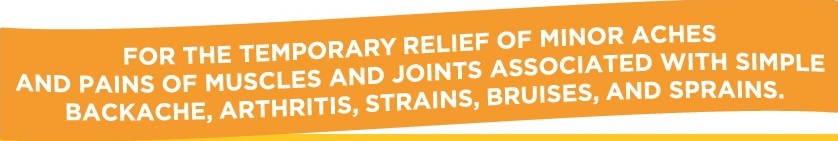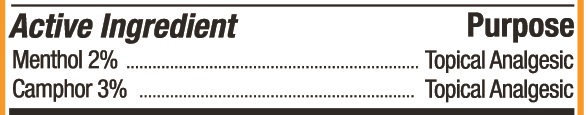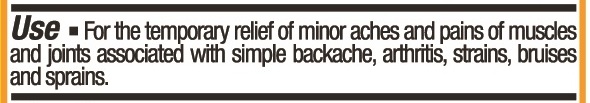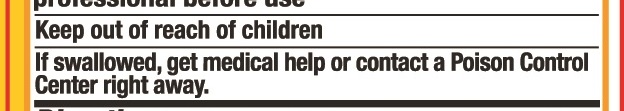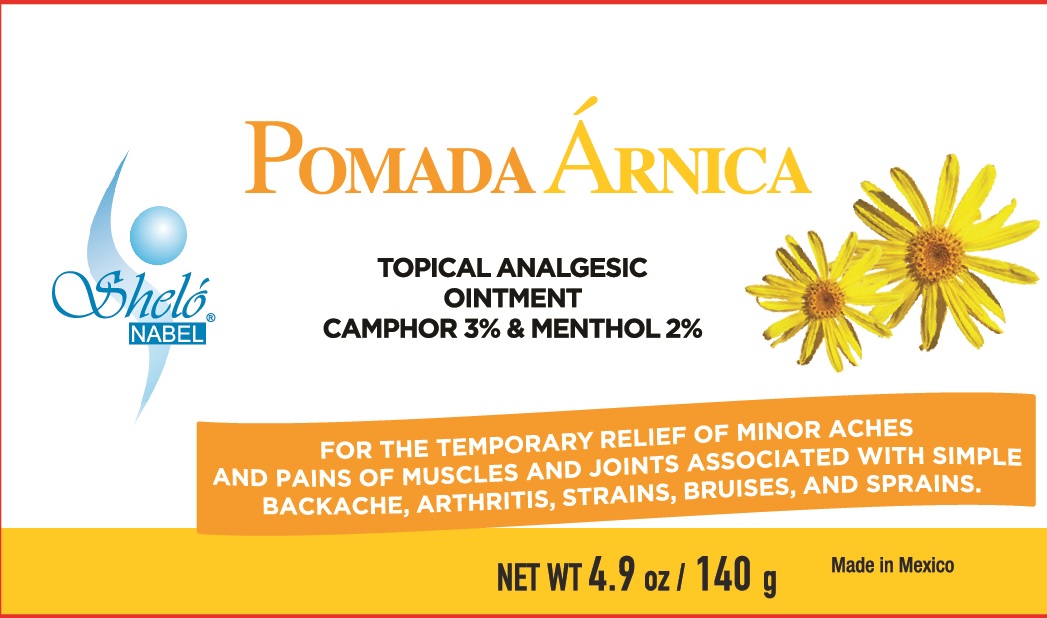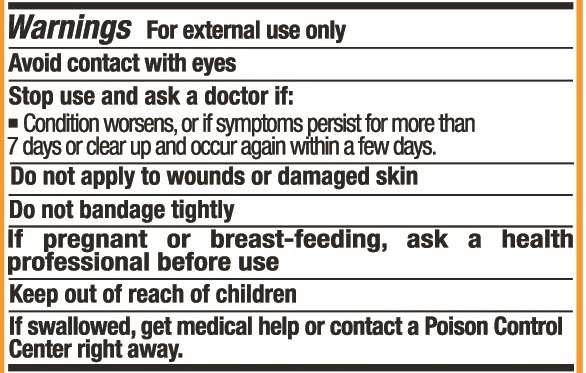 DRUG LABEL: Shelo NABEL Pomada Arnica
NDC: 71424-1059 | Form: GEL
Manufacturer: Corporativo Serysi S de R L de C V
Category: otc | Type: HUMAN OTC DRUG LABEL
Date: 20191015

ACTIVE INGREDIENTS: MENTHOL, UNSPECIFIED FORM 20 mg/1 g; CAMPHOR (SYNTHETIC) 30 mg/1 g
INACTIVE INGREDIENTS: ISOPROPYL PALMITATE

Sheló NABEL Pomada Árnica Gel